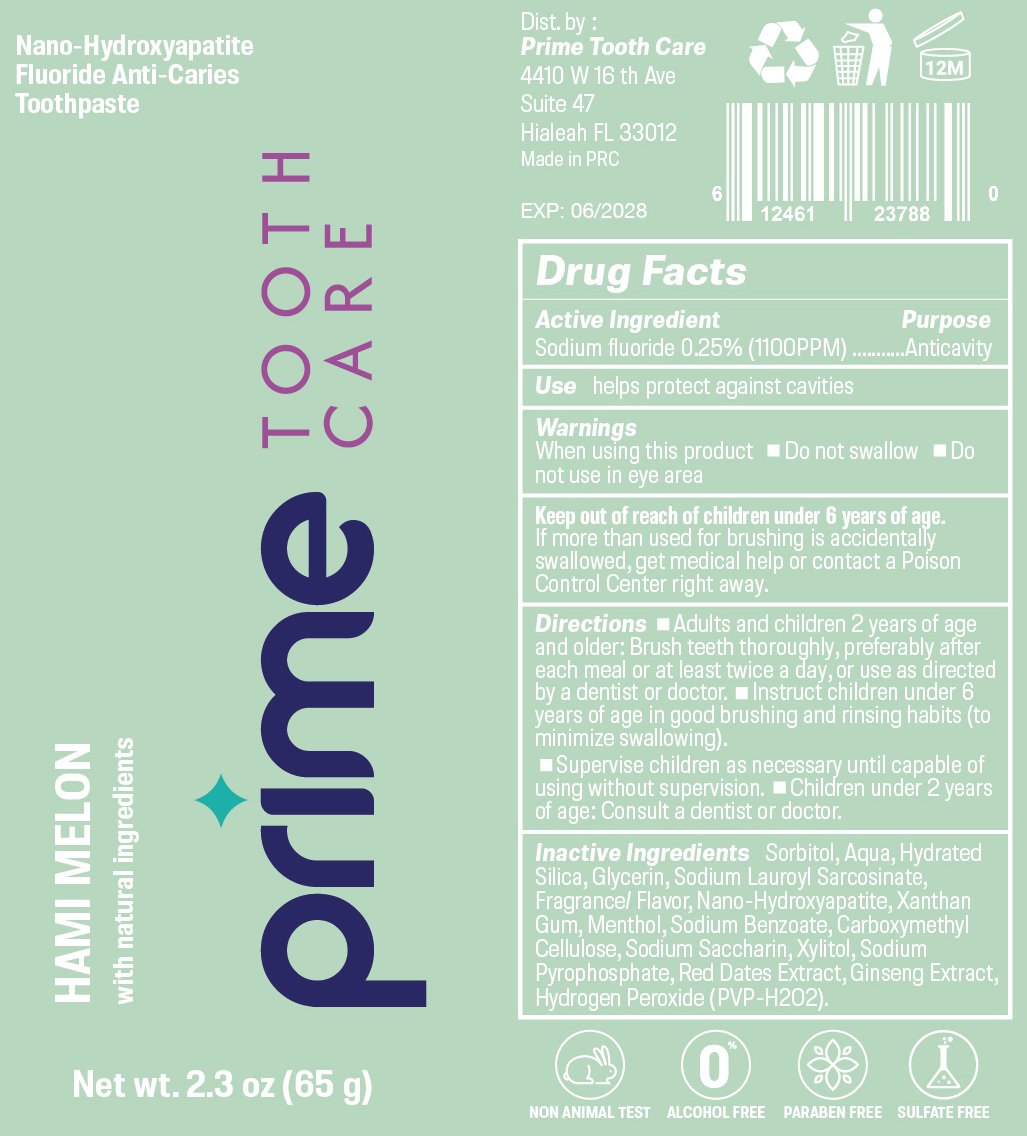 DRUG LABEL: Prime Tooth Care Hami Melon
NDC: 87053-003 | Form: OINTMENT
Manufacturer: Prime Tooth Care LLC
Category: otc | Type: HUMAN OTC DRUG LABEL
Date: 20260109

ACTIVE INGREDIENTS: SODIUM FLUORIDE 2.5 mg/1 g
INACTIVE INGREDIENTS: WATER; HYDRATED SILICA; GLYCERIN; SODIUM LAUROYL SARCOSINATE; XANTHAN GUM; MENTHOL; SODIUM BENZOATE; CARBOXYMETHYLCELLULOSE; SACCHARIN SODIUM; XYLITOL; SODIUM PYROPHOSPHATE; ASIAN GINSENG; HYDROGEN PEROXIDE; SORBITOL

Prime Tooth Care Toothpaste, Hami Melon

Active Ingredient

Sodium fluoride 0.25% (1100PPM)

Purpose

Anticavity

Use

helps protect against cavities

Warnings

When using this product

- Do not swallow
- Do not use in eye area

Keep out of reach of children under 6 years of age.

If more than used for brushing is accidentally swallowed, get medical help or contact a Poison Control Center right away.

Directions

• Adults and children 2 years of age and older: Brush teeth thoroughly, preferably after each meal or at least twice a day, or use as directed by a dentist or doctor. • Instruct children under 6 years of age in good brushing and rinsing habits (to minimize swallowing).

• Supervise children as necessary until capable of using without supervision. • Children under 2 years of age: Consult a dentist or doctor.

Inactive Ingredients

Sorbitol, Aqua, Hydrated Silica, Glycerin, Sodium Lauroyl Sarcosinate, Fragrance/ Flavor, Nano-Hydroxyapatite, Xanthan Gum, Menthol, Sodium Benzoate, Carboxymethyl Cellulose, Sodium Saccharin, Xylitol, Sodium Pyrophosphate, Red Dates Extract, Ginseng Extract, Hydrogen Peroxide (PVP - H202).